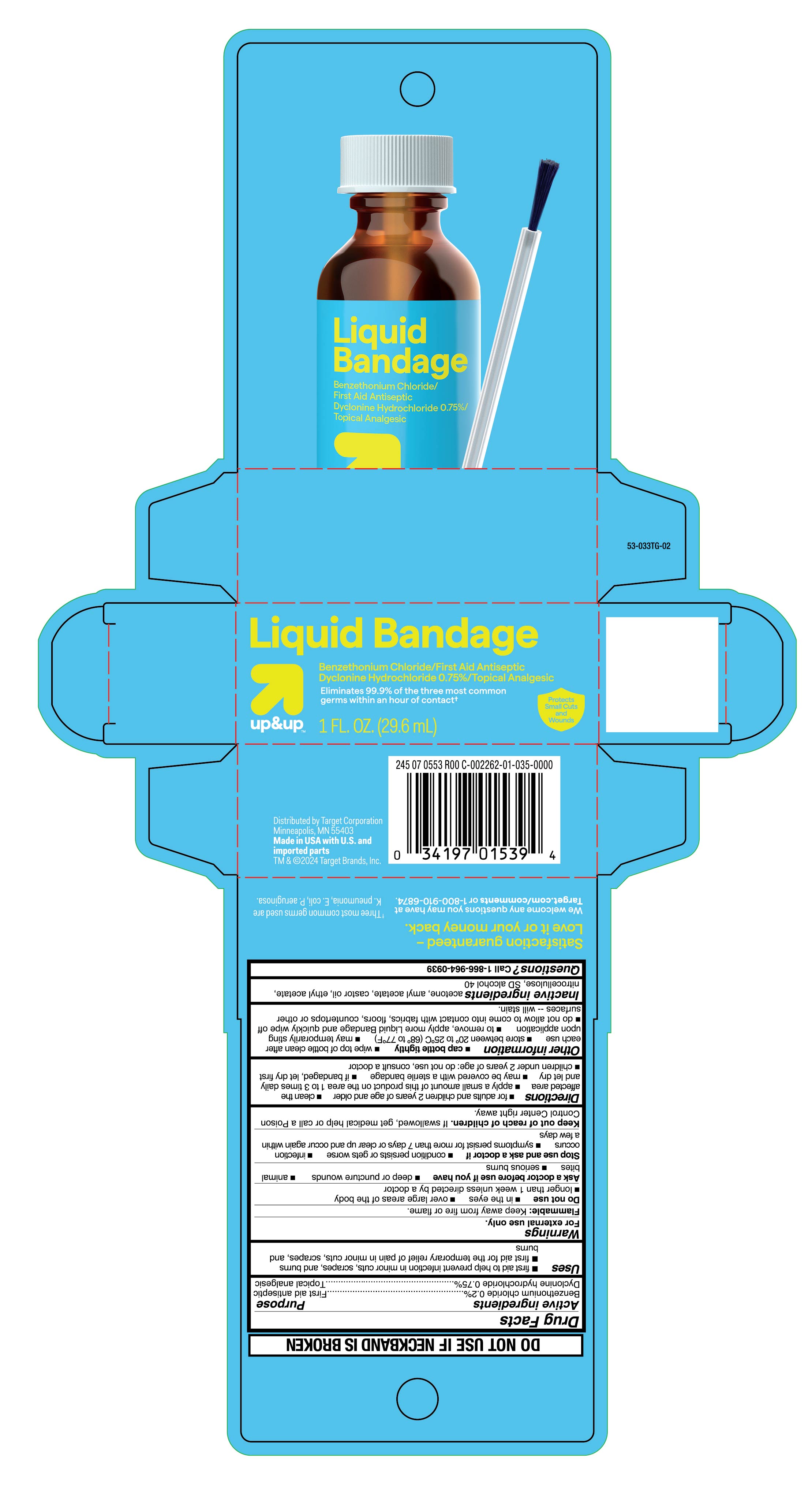 DRUG LABEL: Benzethonium chloride and Dyclonine hydrochloride
NDC: 82442-019 | Form: LIQUID
Manufacturer: Target Corporation
Category: otc | Type: HUMAN OTC DRUG LABEL
Date: 20251007

ACTIVE INGREDIENTS: BENZETHONIUM CHLORIDE 2 mg/1 mL; DYCLONINE HYDROCHLORIDE 7.5 mg/1 mL
INACTIVE INGREDIENTS: AMYL ACETATE; ACETONE; CASTOR OIL; ETHYL ACETATE; PYROXYLIN; ALCOHOL

Target Liquid Bandage

Active ingredients

Benzethonium chloride 0.2%
Dyclonine hydrochloride 0.75%

Purpose

First aid antiseptic
Topical analgesic

Uses

- first aid to help prevent infection in minor cuts, scrapes and burns
- first aid for the temporary relief of pain in minor cuts, scrapes, and burns

Warnings

For external use only.

Flammable:

Keep away from fire or flame.

Do not use

- in the eyes
- over large areas of the body
- longer than 1 week unless directed by a doctor

Ask a doctor before use if you have

- deep or puncture wounds
- animal bites
- serious burns

Stop use and ask a doctor if

- conditions persists or gets worse
- infection occurs
- symptoms persist for more than 7 days or clear up and occur again within a few days

Keep out of reach of children.

If swallowed, get medical help or call a Poison Control Center right away.

When using this product

- do not sotre at temperaure above 120oF

Intentional misuse by deliberately concentrating and inhaling the contents can be harmful or fatal.

Directions

- for adults and children 2 years of age and older
- clean the affected area
- apply a small amount of this product on the area 1-3 times daily and let dry
- may be covered with a sterile bandage
- if bandaged, let dry first
- children under 2 years of age: do not use, consult doctor

Other information

- cap bottle tightly
- wipe top of bottle clean after each use
- store between 20^0 to 25^0C (68^0 to 77^0F)
- may temporarily sting upon application
- to remove, apply more Liquid Bandage and quickly wipe off
- do not allow to come into contact with fabrics, floors, countertops, or other surfaces - will stain

Inactive ingredients

acetone, amyl acetate, castor oil, ethyl acetate, nitrocellulose, SD slcohol 40

Questions

Call 1-866-964-0939

Principal Display Panel

Liquid Bandage

Benzethonium chloride/First Aid Antiseptic
Dyclonine hydrochloride 0.75%/ Topical Analgesic

Eliminates 99.9% of the three most common

germs within an hour of contact

1 FL. OZ. (29.6 mL)